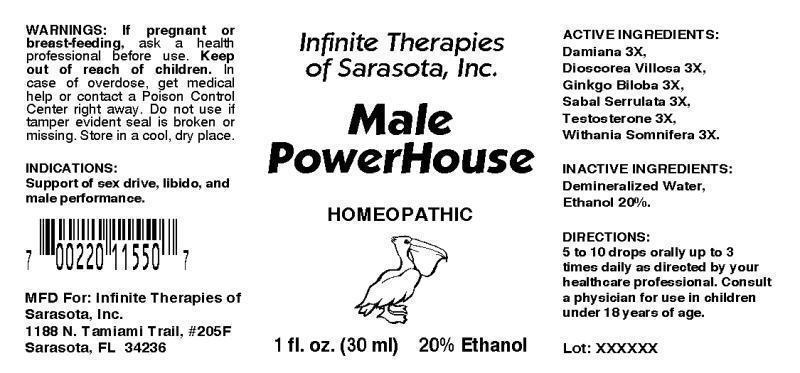 DRUG LABEL: MALE POWERHOUSE
NDC: 54005-0002 | Form: LIQUID
Manufacturer: Infinite Therapies of Sarasota, Inc.
Category: homeopathic | Type: HUMAN OTC DRUG LABEL
Date: 20130812

ACTIVE INGREDIENTS: TURNERA DIFFUSA LEAFY TWIG 3 [hp_X]/1 mL; DIOSCOREA VILLOSA TUBER 3 [hp_X]/1 mL; GINKGO 3 [hp_X]/1 mL; SAW PALMETTO 3 [hp_X]/1 mL; TESTOSTERONE 3 [hp_X]/1 mL; WITHANIA SOMNIFERA ROOT 3 [hp_X]/1 mL
INACTIVE INGREDIENTS: WATER; ALCOHOL

DRUG FACTS:

INDICATIONS:

Support of sex drive, libido, and male performance.

WARNINGS:

If pregnant or breast-feeding, ask a health professional before use.

Keep out of reach of children. In case of overdose, get medical help or contact a Poison Control Center right away.

Do not use if tamper evident seal is broken or missing.

STORAGE:

Store in a cool, dry place.

DIRECTIONS:

5 to 10 drops orally up to 3 times daily as directed by your health care professional. Consult a physician for use in children under 18 years of age.

INACTIVE INGREDIENTS:

Demineralized Water, Ethanol 20%

Keep out of reach of children. In case of overdose, get medical halp or contact a Poison Control Center right away.

INDICATIONS:

Support of sex drive, libido, and male performance.

QUESTIONS:

MFD For: Infinite Therapies of Sarasota, Inc.

1188 N. Tamiami Trail, #205F

Sarasota, FL 34236

PACKAGE DISPLAY LABEL:

Infinite Therapies of Sarasota, Inc.

Male PowerHouse

HOMEOPATHIC

1 fl. oz. (30 mL)